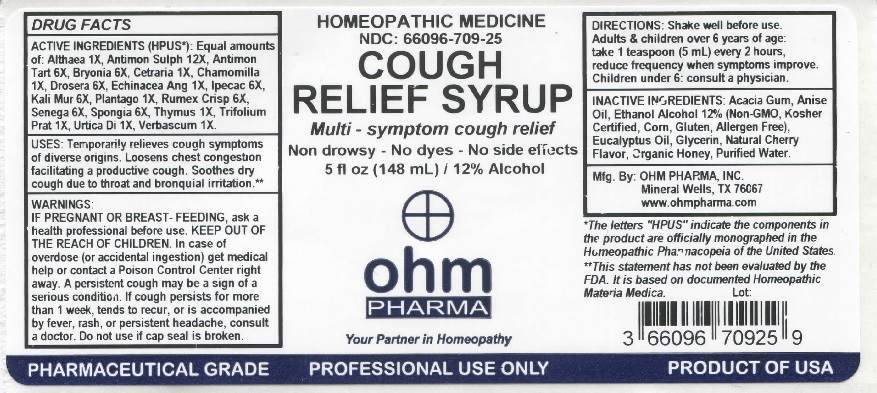 DRUG LABEL: Cough Relief Syrup
NDC: 66096-709 | Form: LIQUID
Manufacturer: OHM PHARMA INC.
Category: homeopathic | Type: HUMAN OTC DRUG LABEL
Date: 20211229

ACTIVE INGREDIENTS: ALTHAEA OFFICINALIS ROOT 1 [hp_X]/148 mL; ANTIMONY PENTASULFIDE 12 [hp_X]/148 mL; ANTIMONY POTASSIUM TARTRATE 6 [hp_X]/148 mL; BRYONIA ALBA ROOT 6 [hp_X]/148 mL; CETRARIA ISLANDICA SUBSP. ISLANDICA 1 [hp_X]/148 mL; MATRICARIA RECUTITA 1 [hp_X]/148 mL; DROSERA ROTUNDIFOLIA 6 [hp_X]/148 mL; ECHINACEA ANGUSTIFOLIA 1 [hp_X]/148 mL; IPECAC 6 [hp_X]/148 mL; POTASSIUM CHLORIDE 6 [hp_X]/148 mL; PLANTAGO LANCEOLATA POLLEN 1 [hp_X]/148 mL; RUMEX CRISPUS ROOT 6 [hp_X]/148 mL; POLYGALA SENEGA ROOT 6 [hp_X]/148 mL; SPONGIA OFFICINALIS SKELETON, ROASTED 6 [hp_X]/148 mL; SUS SCROFA THYMUS 1 [hp_X]/148 mL; TRIFOLIUM PRATENSE FLOWER 1 [hp_X]/148 mL; URTICA DIOICA 1 [hp_X]/148 mL; VERBASCUM THAPSUS 1 [hp_X]/148 mL
INACTIVE INGREDIENTS: ACACIA; ANISE OIL; ALCOHOL; EUCALYPTUS OIL; GLYCERIN; CHERRY; HONEY; WATER

OHM Cough Relief Syrup

ACTIVE INGREDIENT

ACTIVE INGREDIENTS (HPUS*): Equal amounts of: Althaea 1X, Antimon Sulph 12X, Antimon Tart 6X, Bryonia 6X, Cetraria 1X, Chamomilla 1X, Drosera 6X, Echinacea Ang 1X, Ipecac 6X, Kali Mur 6X, Plantago 1X, Rumex Crisp 6X, Senega 6X, Spongia 6X, Thymus 1X, Trifolium Prat 1X, Urtica Di 1X, Verbascum 1X.

* The letters "HPUS" indicate that the components in the product are officially monographed in the Homeopathic Pharmacopeia of the United States.

INDICATIONS AND USAGE

USES: Temporarily relieves cough symptoms of diverse origins. Loosens chest congestion facilitating a productive cough. Soothes dry cough due to throat and bronquial irritation.**

* *This statement has not been evaluated by the FDA. It is based on documented Homeopathic Materia Medica.

WARNINGS

WARNINGS: IF PREGNANT OR BREAST-FEEDING, ask a health care professional before use. In case of overdose (or accidental ingestion) get medical help or contact a Poison Control Center right away. A persistent cough may be a sign of a serious condition. If cough persists for more than 1 week, tends to recur, or is accompanied by fever, rash, or persistent headache, consult a doctor.

- KEEP OUT OF REACH OF CHILDREN.

DOSAGE AND ADMINISTRATION

DIRECTIONS: Shake well before use. Adults & children over 6 years of age: take 1 teaspoon (5mL) every 2 hours, reduce frequency when symptoms improve. Children under 6: consult a physician.

Do not use if cap seal is broken.

INACTIVE INGREDIENT

INACTIVE INGREDIENTS: Acacia Gum, Anise Oil, Ethanol Alcohol 12% (Non-GMO, Kosher Certified, Corn, Gluten, Allergen Free), Eucalyptus Oil, Glycerin, Natural Cherry Flavor, Organic Honey, Purified Water.

QUESTIONS

Mfg By: OHM PHARMA, INC. Mineral Wells, TX 76067

www.ohmpharma.com

PACKAGE LABEL

HOMEOPATHIC MEDICINE

NDC:66096-709-25

COUGH RELIEF SYRUP

Multi - symptom cough relief

Non drowsy - No dyes - No side effects

5 fl oz (148 mL) / 12% Alcohol

PRODUCT OF USA

PURPOSE

Temporarily relieves cough symptoms of diverse origins.